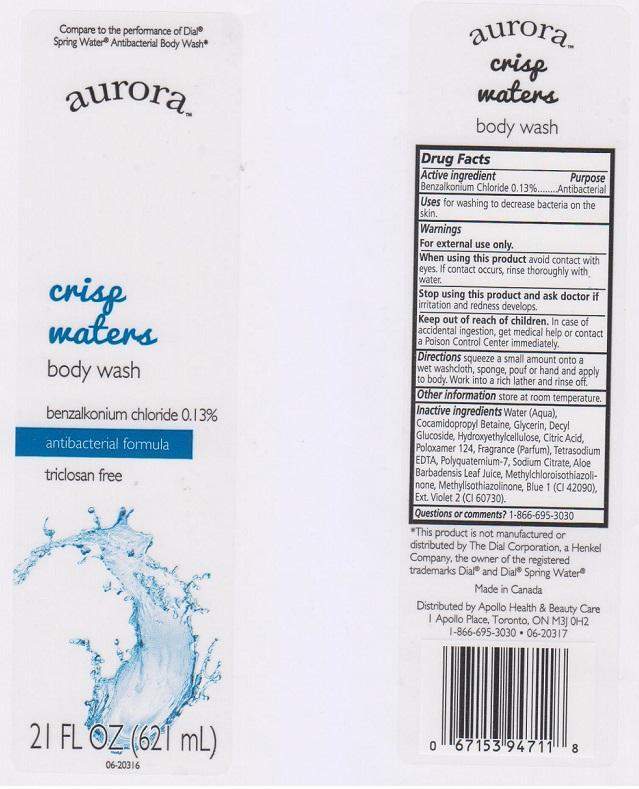 DRUG LABEL: AURORA
NDC: 63148-807 | Form: LIQUID
Manufacturer: APOLLO HEALTH AND BEAUTY CARE
Category: otc | Type: HUMAN OTC DRUG LABEL
Date: 20150304

ACTIVE INGREDIENTS: BENZALKONIUM CHLORIDE 1.3 mg/1 mL
INACTIVE INGREDIENTS: WATER; COCAMIDOPROPYL BETAINE; GLYCERIN; DECYL GLUCOSIDE; HYDROXYETHYL CELLULOSE (5000 CPS AT 1%); CITRIC ACID MONOHYDRATE; POLOXAMER 124; EDETATE SODIUM; POLYQUATERNIUM-7 (70/30 ACRYLAMIDE/DADMAC; 1600000 MW); SODIUM CITRATE; ALOE VERA LEAF; METHYLCHLOROISOTHIAZOLINONE; METHYLISOTHIAZOLINONE; FD&C BLUE NO. 1; D&C VIOLET NO. 2

DRUG FACTS

ACTIVE INGREDIENT

BENZALKONIUM CHLORIDE 0.13%

PURPOSE

ANTIBACTERIAL

USES

FOR WASHING TO DECREASE BACTERIA ON THE SKIN

WARNINGS

FOR EXTERNAL USE ONLY

WHEN USING THIS PRODUCT

AVOID CONTACT WITH EYES. IF CONTACT OCCURS, RINSE THOROUGHLY WITH WATER

STOP USING THIS PRODUCT AND ASK DOCTOR IF

IRRITATION AND REDNESS DEVELOPS

KEEP OUT OF REACH OF CHILDREN

IN CASE OF ACCIDENTAL INGESTION, GET MEDICAL HELP OR CONTACT A POISON CONTROL CENTER IMMEDIATELY

DIRECTIONS

SQUEEZE A SMALL AMOUNT ONTO A WET WASHCLOTH, SPONGE, POUF OR HAND AND APPLY TO BODY. WORK INTO A RICH LATHER AND RINSE OFF

OTHER INFORMATION

STORE AT ROOM TEMPERATURE

INACTIVE INGREDIENTS

WATER (AQUA), COCAMIDOPROPYL BETAINE, GLYCERIN, DECYL GLUCOSIDE, HYDROXYETHYLCELLULOSE, CITRIC ACID, POLOXAMER 124, FRAGRANCE (PARFUM), TETRASODIUM EDTA, POLYQUATERNIUM-7, SODIUM CITRATE, ALOE BARBADENSIS LEAF JUICE, METHYLCHLOROISOTHIAZOLINONE, METHYLISOTHIAZOLINONE, BLUE 1 (CI 42090), EXT. VIOLET 2 (CI 60730)

QUESTIONS OR COMMENTS?

1-866-695-3030